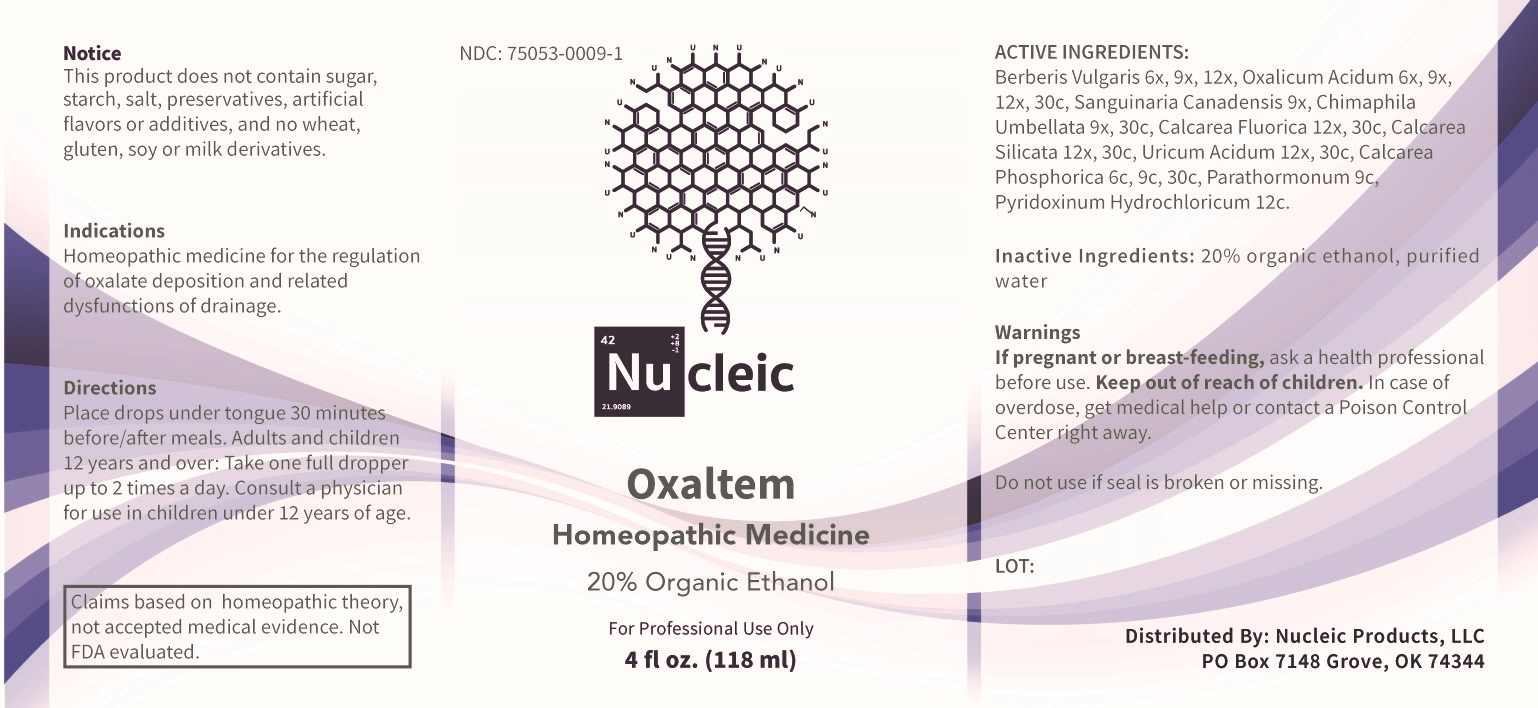 DRUG LABEL: Oxaltem
NDC: 75053-0009 | Form: LIQUID
Manufacturer: Nucleic Products, LLC
Category: homeopathic | Type: HUMAN OTC DRUG LABEL
Date: 20240513

ACTIVE INGREDIENTS: BERBERIS VULGARIS ROOT BARK 6 [hp_X]/1 mL; OXALIC ACID 6 [hp_X]/1 mL; SANGUINARIA CANADENSIS WHOLE 9 [hp_X]/1 mL; CHIMAPHILA UMBELLATA WHOLE 9 [hp_X]/1 mL; CALCIUM FLUORIDE 12 [hp_X]/1 mL; CALCIUM SILICATE 12 [hp_X]/1 mL; URIC ACID 12 [hp_X]/1 mL; TRIBASIC CALCIUM PHOSPHATE 6 [hp_C]/1 mL; PARATHYROID HORMONE 9 [hp_C]/1 mL; PYRIDOXINE HYDROCHLORIDE 12 [hp_C]/1 mL
INACTIVE INGREDIENTS: WATER; ALCOHOL

DRUG FACTS:

ACTIVE INGREDIENTS:

Berberis Vulgaris 6X, 9X, 12X, Oxalicum Acidum 6X, 9X, 12X, 30C, Sanguinaria Canadensis 9X, Chimaphila Umbellata 9X, 30C, Calcarea Fluorica 12X 30C, Calcarea Silicata 12X 30C, Uricum Acidum 12X, 30C, Calcarea Phosphorica 6C, 9C, 30C, Parathormonum 9C, Pyridoxinum Hydrochloricum 12C,

INDICATIONS:

Homeopathic medicine for the regulation of oxalate deposition and related dysfunctions of drainage.

Claims based on homeopathic theory, not accepted medical evidence. Not FDA evaluated.

WARNINGS:

If pregnant or breast-feeding, ask a health professional before use.

Keep out of reach of children. In case of overdose, get medical help or contact a Poison Control Center right away.

Do not use if seal is broken or missing.

This Product does not contain sugar, starch, salt, preservatives, artificial flavors or additives, and no wheat, gluten, soy or milk derivatives.

KEEP OUT OF REACH OF CHILDREN:

In case of overdose, get medical help or contact a Poison Control Center right away.

DIRECTIONS:

Place drops under tongue 30 minutes before/after meals. Adults and children 12 years and over: Take one full dropper up to 2 times a day. Consult a physician for use in children under 12 years of age.

INDICATIONS:

Homeopathic medicine for the regulation of oxalate deposition and related dysfunctions of drainage.

Claims based on homeopathic theory, not accepted medical evidence. Not FDA evaluated.

INACTIVE INGREDIENTS

20% organic ethanol, purified water

QUESTIONS:

Distributed by: Nucleic Products, LLC

PO Box 7148 Grove, OK 74344

PACKAGE LABEL DISPLAY:

NDC: 75053-0009-1

Nu cleic

Oxaltem

Homeopathic Medicine

For Professional Use Only

4 fl oz. (118 ml)